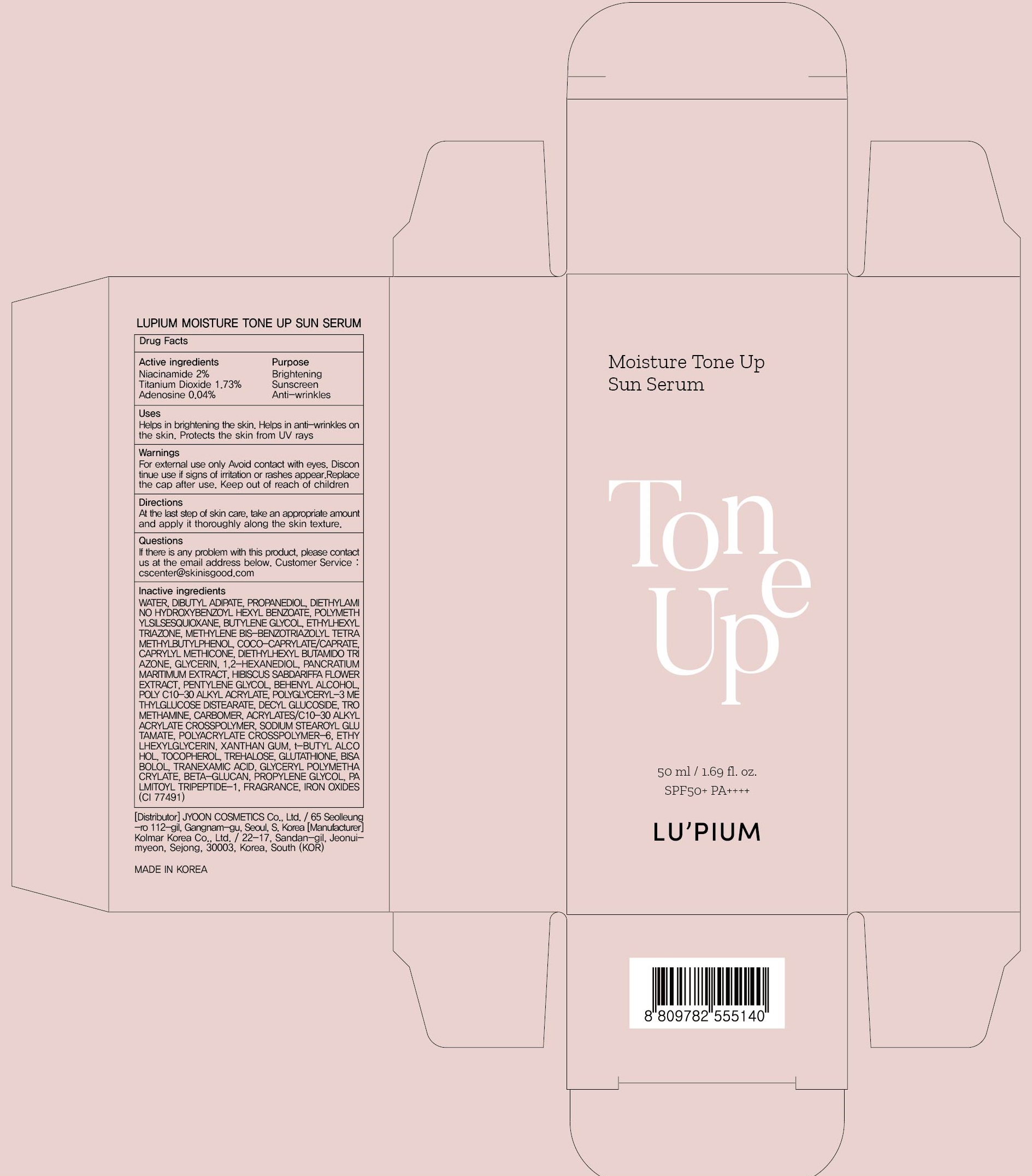 DRUG LABEL: LUPIUM MOISTURE TONE UP SUN SERUM
NDC: 82284-020 | Form: LIQUID
Manufacturer: JYOONCOSMETICS Co, Ltd
Category: otc | Type: HUMAN OTC DRUG LABEL
Date: 20211012

ACTIVE INGREDIENTS: Niacinamide 1.00 g/50 mL; Titanium Dioxide 0.86 g/50 mL; Adenosine 0.02 g/50 mL
INACTIVE INGREDIENTS: Water; Dibutyl Adipate

ACTIVE INGREDIENTS

Niacinamide 2%
Titanium Dioxide 1.73%
Adenosine 0.04%

INACTIVE INGREDIENTS

WATER, DIBUTYL ADIPATE, PROPANEDIOL, DIETHYLAMINO HYDROXYBENZOYL HEXYL BENZOATE, POLYMETHYLSILSESQUIOXANE, BUTYLENE GLYCOL, ETHYLHEXYL TRIAZONE, METHYLENE BIS-BENZOTRIAZOLYL TETRAMETHYLBUTYLPHENOL, COCO-CAPRYLATE/CAPRATE, CAPRYLYL METHICONE, DIETHYLHEXYL BUTAMIDO TRIAZONE, GLYCERIN, 1,2-HEXANEDIOL, PANCRATIUM MARITIMUM EXTRACT, HIBISCUS SABDARIFFA FLOWER EXTRACT, PENTYLENE GLYCOL, BEHENYL ALCOHOL, POLY C10-30 ALKYL ACRYLATE, POLYGLYCERYL-3 METHYLGLUCOSE DISTEARATE, DECYL GLUCOSIDE, TROMETHAMINE, CARBOMER, ACRYLATES/C10-30 ALKYL ACRYLATE CROSSPOLYMER, SODIUM STEAROYL GLUTAMATE, POLYACRYLATE CROSSPOLYMER-6, ETHYLHEXYLGLYCERIN, XANTHAN GUM, t-BUTYL ALCOHOL, TOCOPHEROL, TREHALOSE, GLUTATHIONE, BISABOLOL, TRANEXAMIC ACID, GLYCERYL POLYMETHACRYLATE, BETA-GLUCAN, PROPYLENE GLYCOL, PALMITOYL TRIPEPTIDE-1, FRAGRANCE, IRON OXIDES(CI 77491)

PURPOSE

Brightening, Sunscreen, Anti-wrinkles

WARNINGS

For external use only
Avoid contact with eyes.
Discontinue use if signs of irritation or rashes appear.
Replace the cap after use.
Keep out of reach of children

KEEP OUT OF REACH OF CHILDREN

Uses

Helps in brightening the skin.
Helps in anti-wrinkles on the skin.
Protects the skin from UV rays

Directions

At the last step of skin care, take an appropriate amount and apply it thoroughly along the skin texture.

QUESTIONS

If there is any problem with this product, please contact us at the email address below. Customer Service : cscenter@skinisgood.com